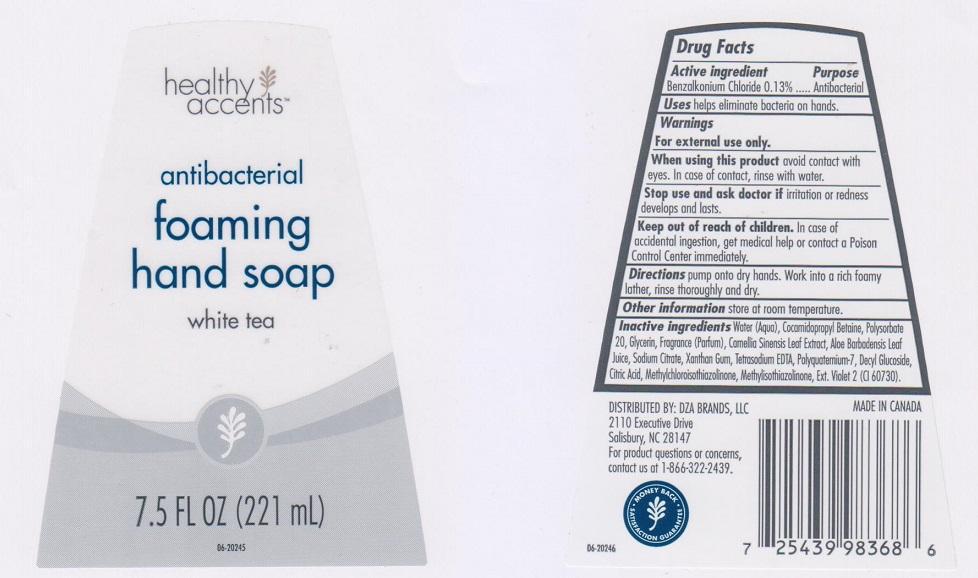 DRUG LABEL: HEALTHY ACCENTS
NDC: 55316-102 | Form: LIQUID
Manufacturer: DZA BRANDS LLC
Category: otc | Type: HUMAN OTC DRUG LABEL
Date: 20150204

ACTIVE INGREDIENTS: BENZALKONIUM CHLORIDE 1.3 mg/1 mL
INACTIVE INGREDIENTS: WATER; COCAMIDOPROPYL BETAINE; POLYSORBATE 20; GLYCERIN; GREEN TEA LEAF; ALOE VERA LEAF; SODIUM CITRATE; XANTHAN GUM; EDETATE SODIUM; POLYQUATERNIUM-7 (70/30 ACRYLAMIDE/DADMAC; 1600000 MW); DECYL GLUCOSIDE; CITRIC ACID MONOHYDRATE; METHYLCHLOROISOTHIAZOLINONE; METHYLISOTHIAZOLINONE; EXT. D&C VIOLET NO. 2

DRUG FACTS

ACTIVE INGREDIENT

BENZALKONIUM CHLORIDE 0.13%

PURPOSE

ANTIBACTERIAL

USES

HELPS ELIMINATE BACTERIA ON HANDS

WARNINGS

FOR EXTERNAL USE ONLY

WHEN USING THIS PRODUCT

AVOID CONTACT WITH EYES. IN CASE OF CONTACT, RINSE WITH WATER

STOP USE AND ASK DOCTOR IF

IRRITATION OR REDNESS DEVELOPS AND LASTS

KEEP OUT OF REACH OF CHILDREN

IN CASE OF ACCIDENTAL INGESTION, GET MEDICAL HELP OR CONTACT A POISON CONTROL CENTER IMMEDIATELY

DIRECTIONS

PUMP ONTO DRY HANDS. WORK INTO A RICH FOAMY LATHER, RINSE THOROUGHLY AND DRY

OTHER INFORMATION

STORE AT ROOM TEMPERATURE

INACTIVE INGREDIENTS

WATER (AQUA), COCAMIDOPROPYL BETAINE, POLYSORBATE 20, GLYCERIN, FRAGRANCE (PARFUM), CAMELLIA SINENSIS LEAF EXTRACT, ALOE BARBADENSIS LEAF JUICE, SODIUM CITRATE, XANTHAN GUM, TETRASODIUM EDTA, POLYQUATERNIUM-7, DECYL GLUCOSIDE, CITRIC ACID, METHYLCHLOROISOTHIAZOLINONE, METHYLISOTHIAZOLINONE, EXT. VIOLET 2 (CI 60730)